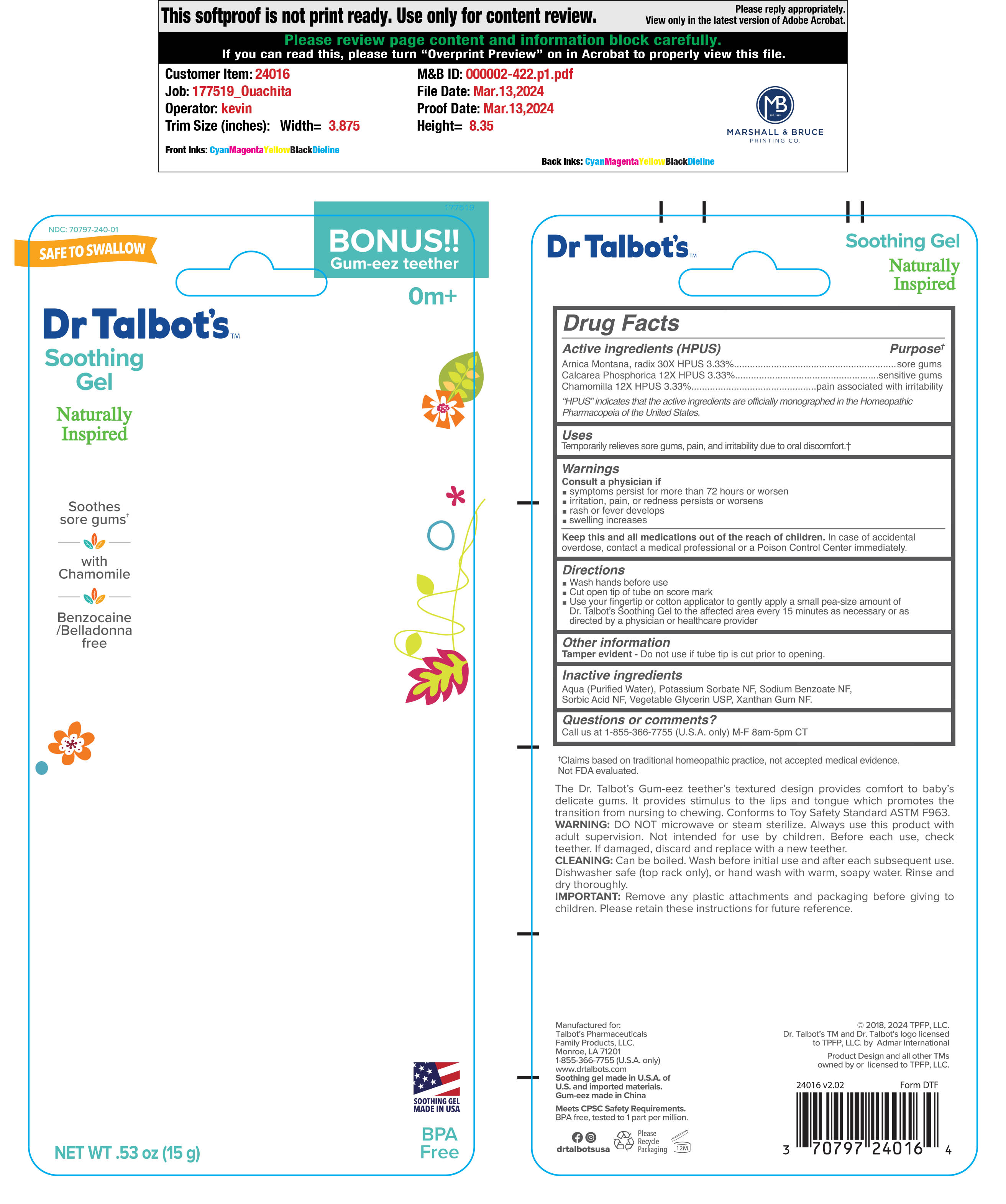 DRUG LABEL: Nuby Soothing Gel
NDC: 70797-240 | Form: GEL
Manufacturer: Talbot's Pharmaceuticals Family Products, LLC.
Category: homeopathic | Type: HUMAN OTC DRUG LABEL
Date: 20250120

ACTIVE INGREDIENTS: MATRICARIA RECUTITA 12 [hp_X]/15 g; ARNICA MONTANA ROOT 30 [hp_X]/15 g; TRIBASIC CALCIUM PHOSPHATE 12 [hp_X]/15 g
INACTIVE INGREDIENTS: SODIUM BENZOATE; WATER; SORBIC ACID; POTASSIUM SORBATE; XANTHAN GUM; GLYCERIN

ACTIVE INGREDIENT

- Arnica Montana, radix 30X HPUS 3.33%

- Calcarea Phosphorica 12 X HPUS 3.33%

- Chamomilla 12X HPUS 3.33%

INACTIVE INGREDIENT

- Aqua (Purified Water)
- Potassium Sorbate NF
- Sodium Benzoate NF
- Sorbic Acid NF
- Vegetable Glycerin USP
- Xantham Gum NF

WARNINGS

Counsult a Physician if

- symptoms persist for more than 72 hours or worsen
- irritation, pain, or redness persists or worsens
- rash or fever develops
- swelling increases

KEEP OUT OF REACH OF CHILDREN

Keep this and all medications out of the reach of children

in case of accidental overdose, contact a medical perffessional or a Poision Control Center immidiately.

Purpose

- soregums
- sensitive gums
- pain ssociated with irritability

Directions

- Wash hands before use
- Cut open tip of tube on score mark
- Use your fingertip or cotton applicator to gently apply a small pea-size amount of Dr. Talbot's Soothing gel to the affected area every 15 minitues as neccessary or as directed by a physician or healthcare provider

Other information

Tamper evident - Do not use if tube is cut prior to opening.

Questions & comments?

Call us at 1-855-366-7755 (U.S.A. only) M-F 8am-5pm CT

PACKAGE LABEL

NDC 70797-240-01 Bonus!!

SAFE TO SWALLOW Gum-eez-teether

Dr Talbot's

Soothing Gel 0m+

Naturally

Inspired

Soothes

sore gums

With

Chamomile

Benzocaine

/Belledonna

free